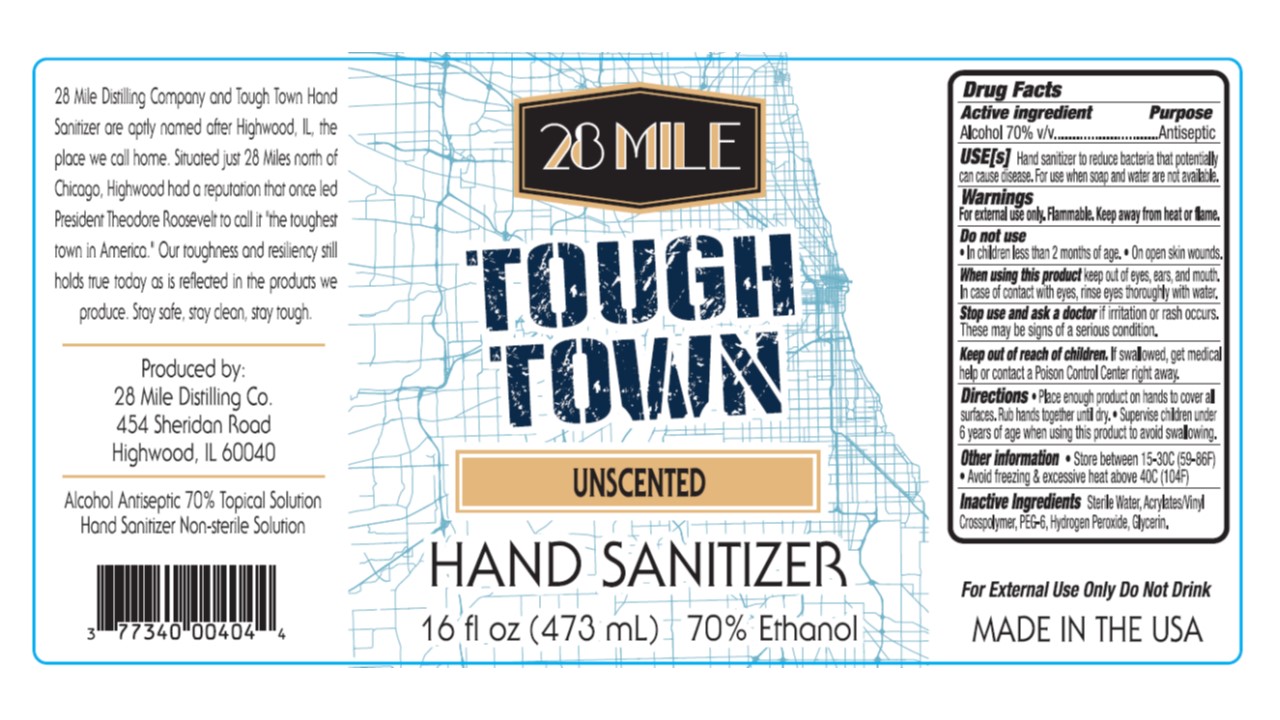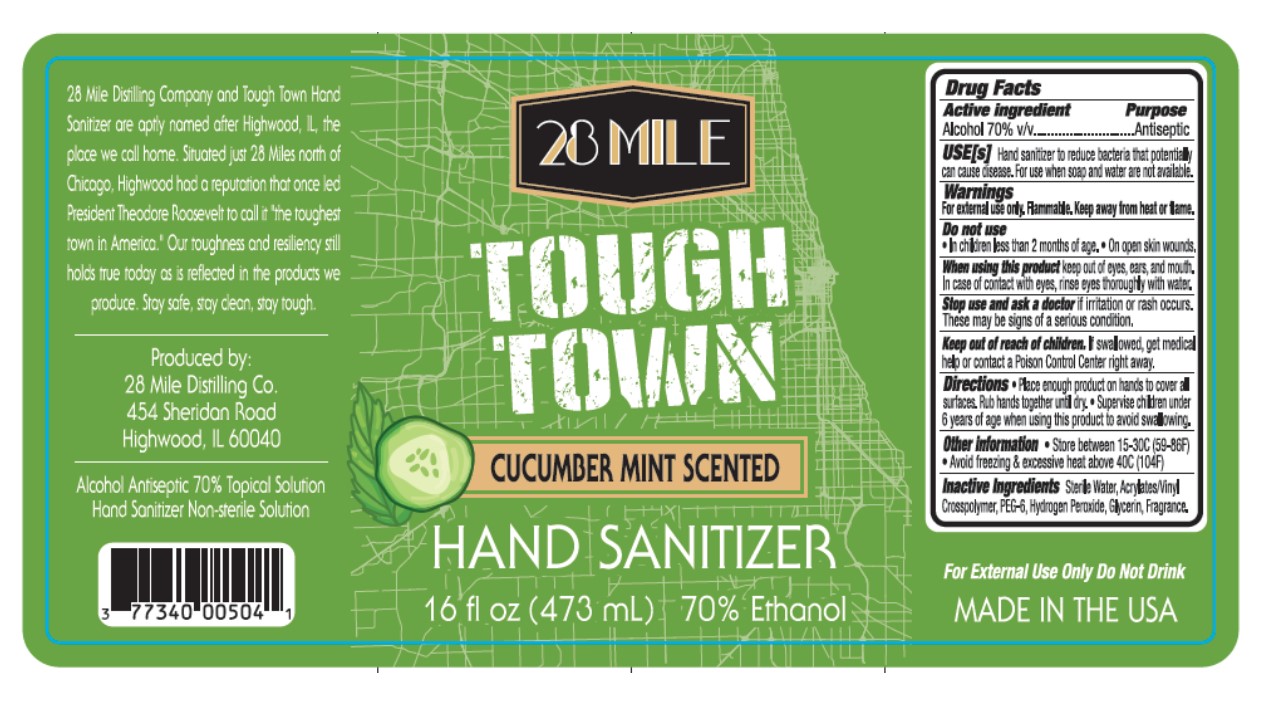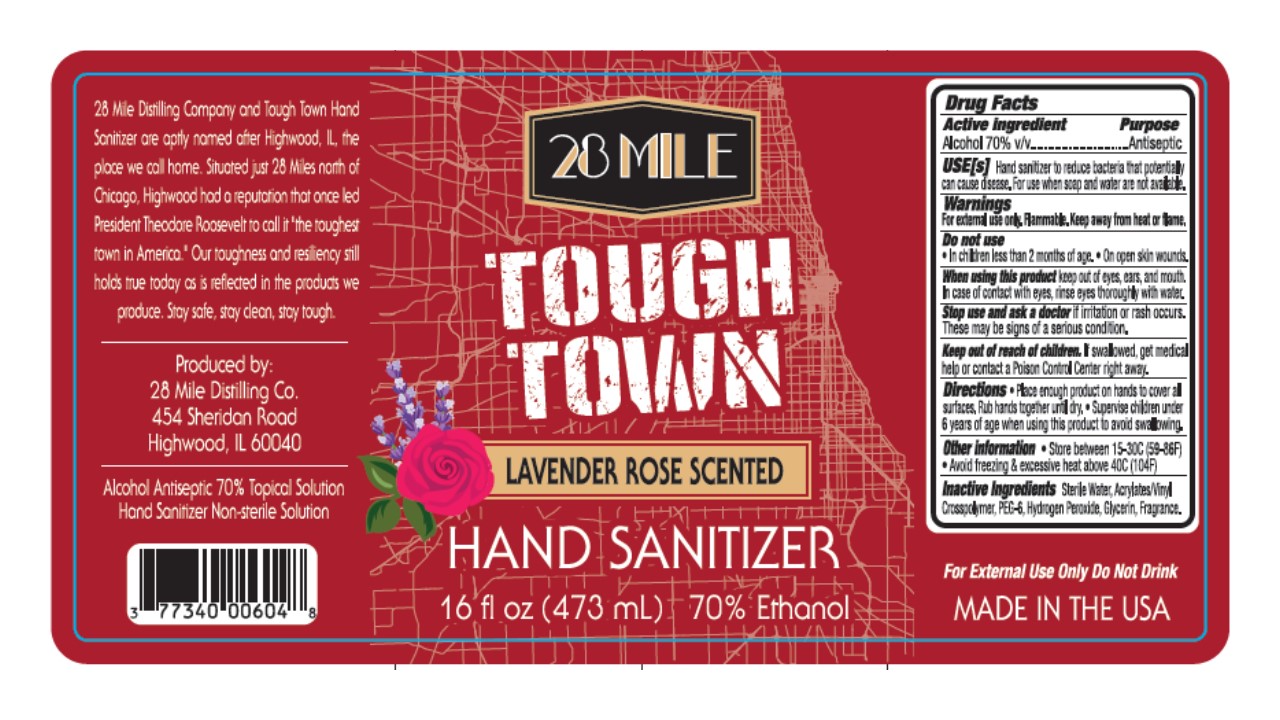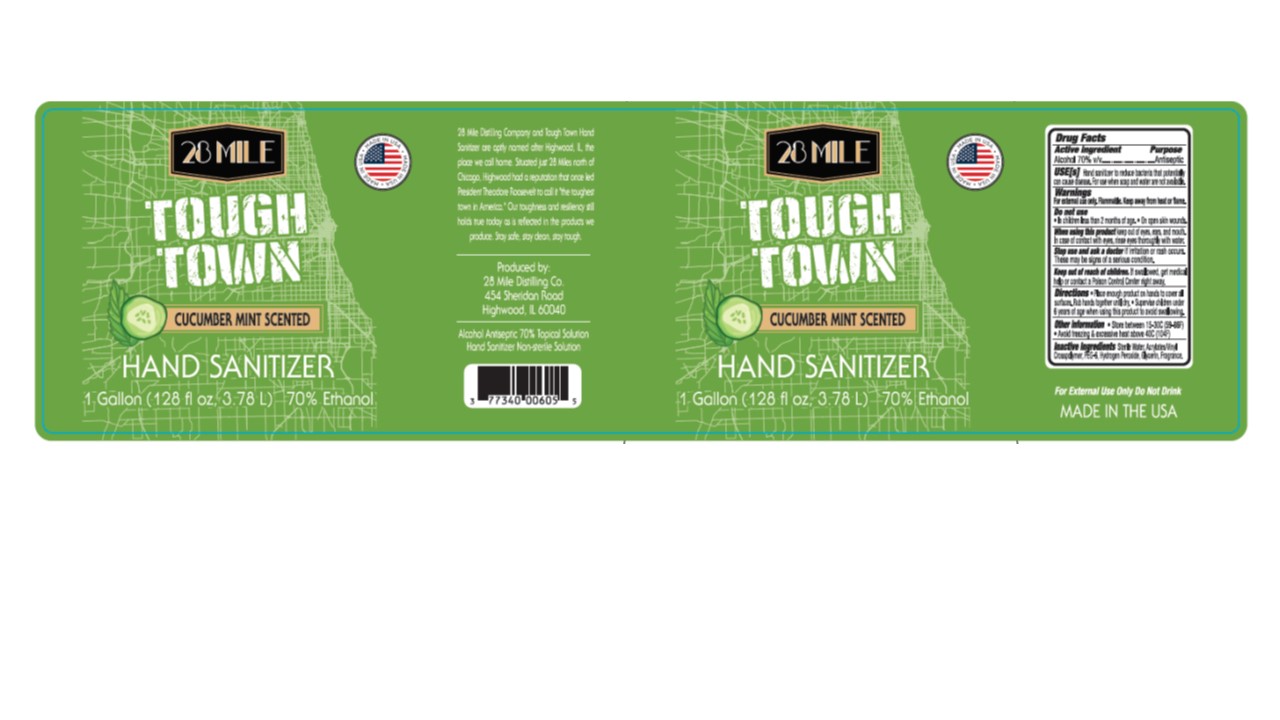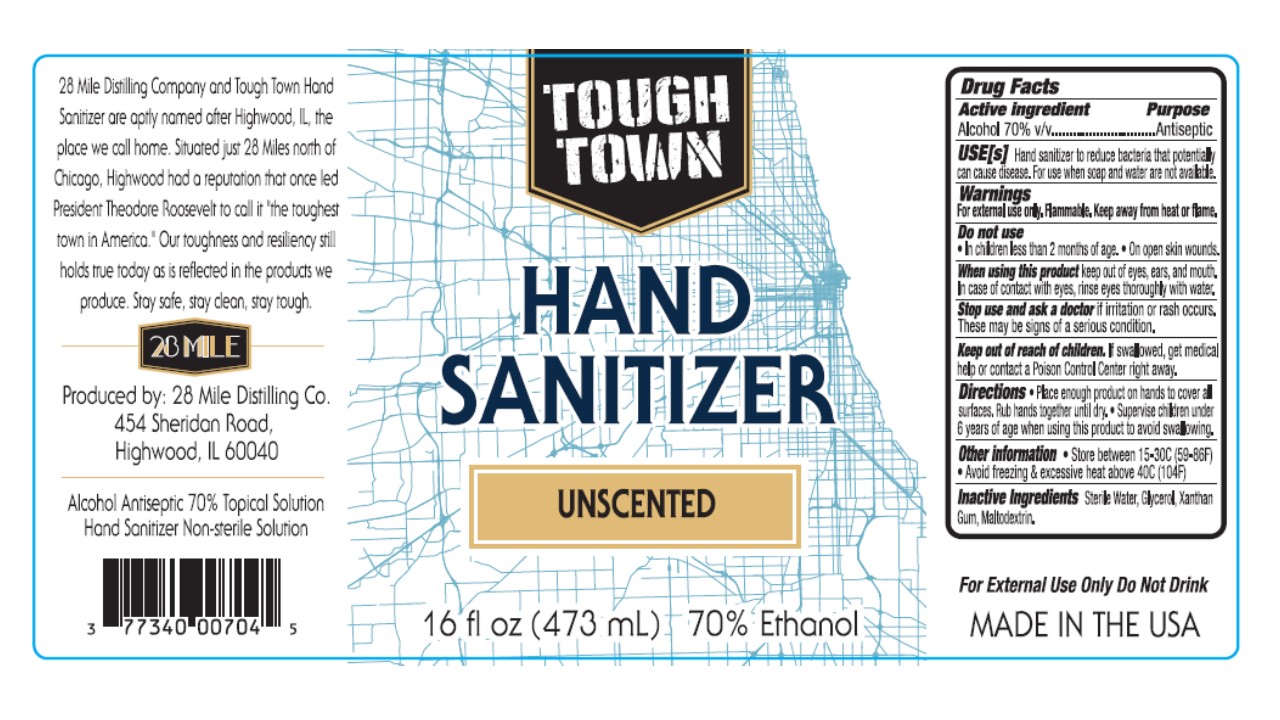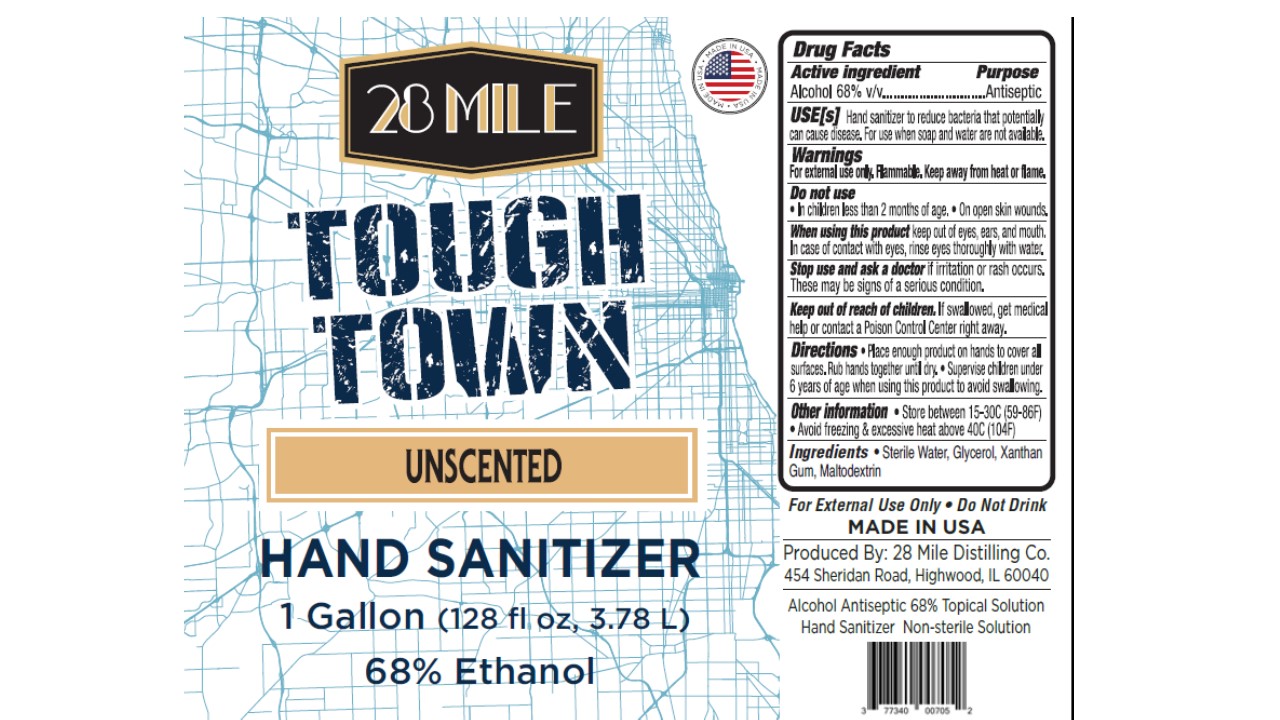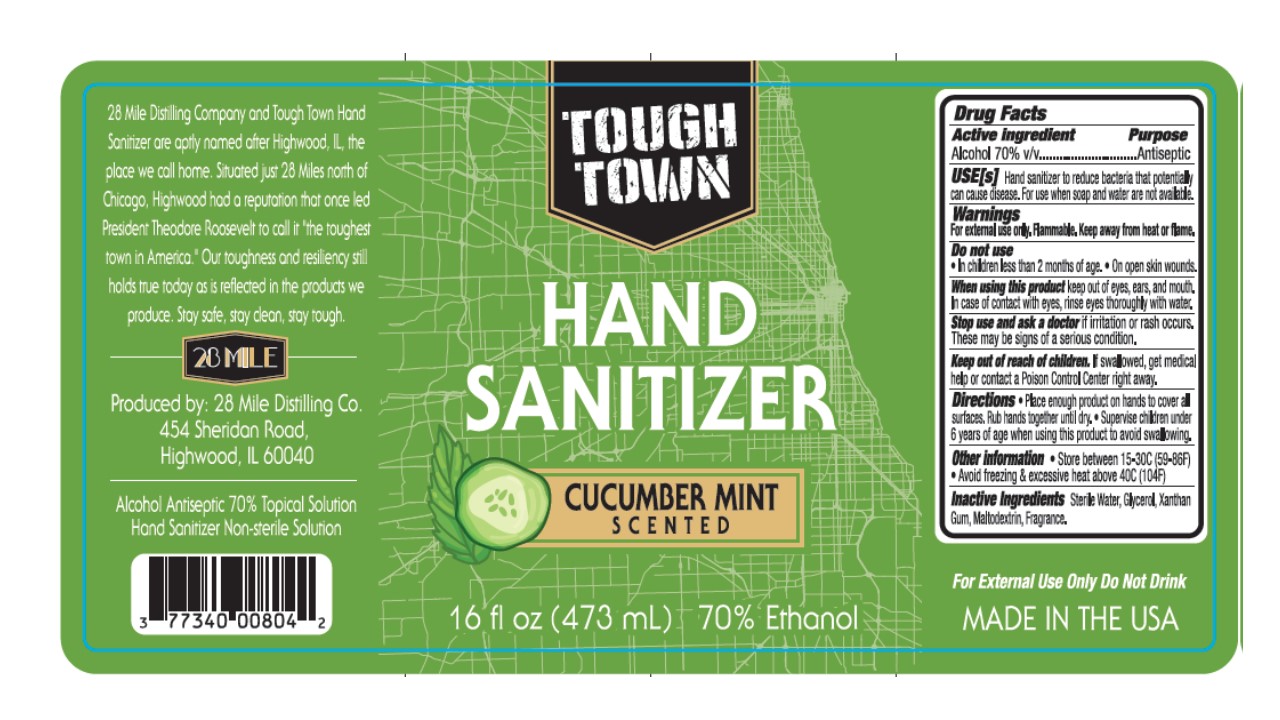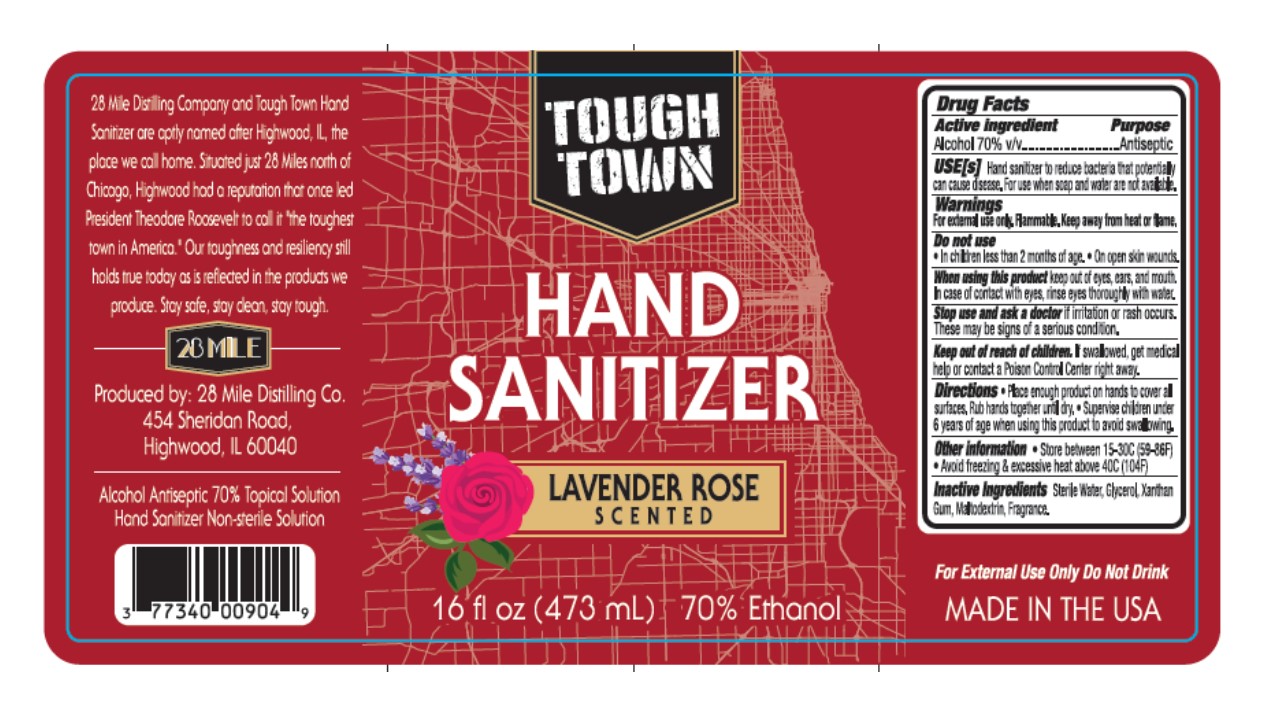 DRUG LABEL: 28 Mile Tough Town Hand Sanitizer
NDC: 77340-004 | Form: GEL
Manufacturer: 28 Mile Vodka Company LLC
Category: otc | Type: HUMAN OTC DRUG LABEL
Date: 20201030

ACTIVE INGREDIENTS: ALCOHOL 70 mL/100 mL
INACTIVE INGREDIENTS: RAPIDGEL EZ1; HYDROGEN PEROXIDE; GLYCERIN; WATER

Drug Facts

Active ingredient

Ethyl Alcohol 70%

Purpose

Hand and Skin Antiseptic

Uses

Hand & Skin Antiseptic to help decrease pathogens (germs) on the skin

Warning

For extgernal use only

Flammable

Keep away from heat or flame

Do not use

* In Children less than 2 months of age

* On open skin wounds

Ask a doctor before use if you have

* Irritation or rash occurs

Stop use and ask docotr if

* redness or skin irritation develop after use.

Keep out of reach of children

Supervise children under 6 years of age when using this product to avoid swallowing

Directions

* Place enough product on hands to cover all surfaces

* Rub Hands together until dry

Inactive ingredients

Water, Glycerine, PEG-6, Acrylates/Vinyl Cross polymer, Polyethylene Glycol, 1,2,3 - Propanetriol, 1,3-Propanediamine, Gycerol, Xanthan Gum, Maltodextrin, Fragrance

Principal Display Panel

28 Mile Tough Town Hand sanitizer

Tough Town Hand Sanitizer

Cumuber Mint Scented

Lavebder Rose Scented

Unscented

For external use only,

Do not Drink

28 Mile Distilling Company and Tough Town Hand Sanitizer are aptly named after Highwood, IL, the place we call home. Situated just 28 miles north of Chicago, Highwood had a reputation that once led President Theodore Roosevelt to call it "the toughest town in America". Out toughness and resiliency still holds true today as is reflected in the products we produce. Stay safe, stay clean, stay tough.

Produce by:

28 Mile Distilling Co.

454 Sheridon Road, Highwood

IL 60040

Alcohol Antiseptic 70% Topical Solution

Hand Sanitizer Non-sterile solution

NDC: 77340-004-xx; 77340-005-xx; 77340-006-xx; 77340-007-xx; 77340-008-xx; 77340-009-xx